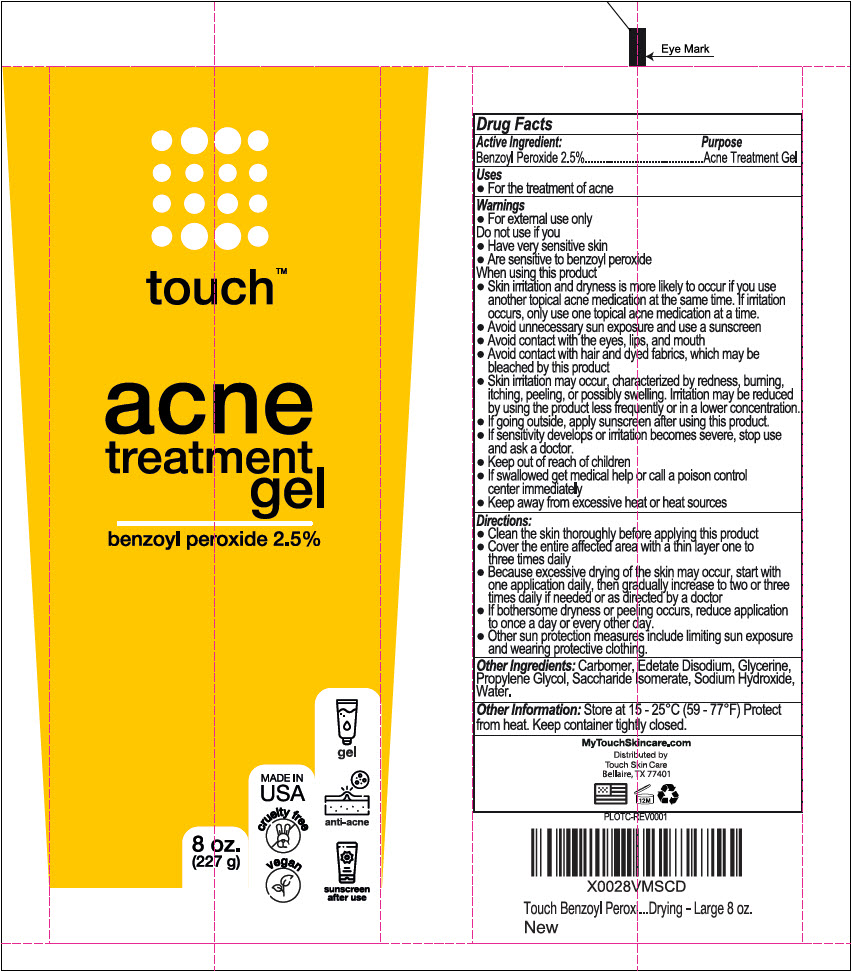 DRUG LABEL: Touch Acne Treatment 
NDC: 73246-001 | Form: GEL
Manufacturer: Diractions Capital LLC
Category: otc | Type: HUMAN OTC DRUG LABEL
Date: 20250703

ACTIVE INGREDIENTS: Benzoyl Peroxide 25 mg/1 g
INACTIVE INGREDIENTS: Water; Glycerin; Propylene Glycol; Edetate Disodium; Sodium Hydroxide; Saccharide Isomerate; Carbomer Homopolymer Type C (Allyl Pentaerythritol Crosslinked)

Touch™ Acne Treatment Gel
Benzoyl Peroxide 2.5%

Drug Facts

Active Ingredient

Benzoyl Peroxide 2.5%

Purpose

Acne Treatment Gel

Uses

- For the treatment of acne

Warnings

- For external use only

Do not use if you

- Have very sensitive skin
- Are sensitive to benzoyl peroxide

When using this product

- Skin irritation and dryness is more likely to occur if you use another topical acne medication at the same time. If irritation occurs, only use one topical acne medication at a time.
- Avoid unnecessary sun exposure and use a sunscreen
- Avoid contact with the eyes, lips, and mouth
- Avoid contact with hair and dyed fabrics, which may be bleached by this product
- Skin irritation may occur, characterized by redness, burning, itching, peeling, or possibly swelling. Irritation may be erduced by using the product less frequently or in a lower concentartion.
- If going outside, apply sunscreen after using this product.
- If sensitivity develops or irritation becomes severe, stop use and ask a doctor

- Keep out of reach of children
- If swallowed get medical help or call a poison control center immediately
- Keep away from excessive heat or heat sources

Directions

- Clean the skin thoroughly before applying this product
- Cover the entire affected area with a thin layer one to three times daily
- Because excessive drying of the skin may occur, start with one application daily, then gradually increase to two or three times daily if needed or as directed by a doctor
- If bothersome dryness or peeling occurs, reduce application to once a day or every other day.
- Other sun protection measures include limiting sun exposure and wearing protective clothing.

Other Ingredients

Carbomer, Edetate Disodium, Glycerine, Propylene Glycol, Saccharide Isomerate, Sodium Hydroxide, Water.

Other Information

Store at 15 - 25°C (59 - 77°F) Protect from heat. Keep container tightly closed.

Distributed by
Touch Skin Care
Bellaire, TX 77401

PRINCIPAL DISPLAY PANEL - 227 g Tube Label

touch™

acne
treatment
gel

benzoyl peroxide 2.5%

8 oz.
(227 g)

MADE IN
USA

cruelty free

vegan

gel

anti-acne

sunscreen
after use